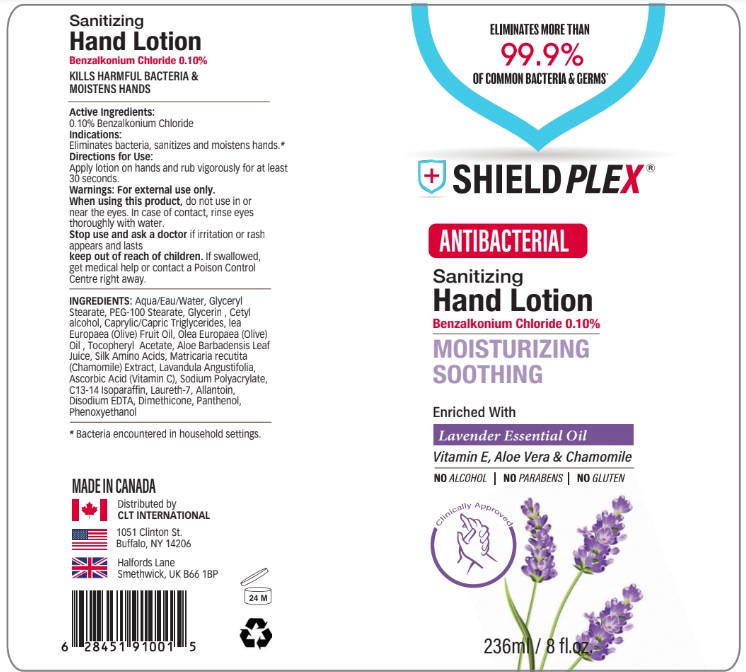 DRUG LABEL: Shieldplex
NDC: 75490-002 | Form: LOTION
Manufacturer: CLT Logistics Inc.
Category: otc | Type: HUMAN OTC DRUG LABEL
Date: 20200612

ACTIVE INGREDIENTS: BENZALKONIUM CHLORIDE 0.1 g/100 mL
INACTIVE INGREDIENTS: WATER; GLYCERYL MONOSTEARATE; PEG-100 STEARATE; OLIVE OIL; MEDIUM-CHAIN TRIGLYCERIDES; GLYCERIN; CETYL ALCOHOL; OLEA EUROPAEA (OLIVE) OIL UNSAPONIFIABLES; SODIUM POLYACRYLATE (8000 MW); C13-14 ISOPARAFFIN; LAURETH-7; ALLANTOIN; EDETATE DISODIUM ANHYDROUS; DIMETHICONE; ALOE VERA LEAF; .ALPHA.-TOCOPHEROL ACETATE; BUTYLATED HYDROXYTOLUENE; LAVANDULA ANGUSTIFOLIA SUBSP. ANGUSTIFOLIA FLOWER; CHAMOMILE; AMINO ACIDS, SILK; PANTHENOL

Active Ingredient

0.10% Benzalkonium Chloride

Indications

Eliminates bacteria, sanitizes and moistens hands.

Warnings

For external use only.
When using this product, do not use in or near the eyes. In case of contact, rinse eyes thoroughly with water.
Stop use and ask a doctor if irritation or rash appears and lasts.

Keep out of reach of children. If swallowed, get medical help or contact a Poison Control Center right away.

Directions for use

Apply lotion on hands and rub vigorously for at least 30 seconds.

Inactive ingredients

Aqua/Eau/Water, Glyceryl Stearate, PEG-100 Stearate, Glycerin , Cetyl alcohol, Caprylic/Capric Triglycerides, lea Europaea (Olive) Fruit Oil, Olea Europaea (Olive) Oil , Tocopheryl Acetate, Aloe Barbadensis Leaf Juice, Silk Amino Acids, Matricaria recutita (Chamomile) Extract, Lavandula Angustifolia, Ascorbic Acid (Vitamin C), Sodium Polyacrylate, C13-14 Isoparaffin, Laureth-7, Allantoin, Disodium EDTA, Dimethicone, Panthenol, Phenoxyethanol.